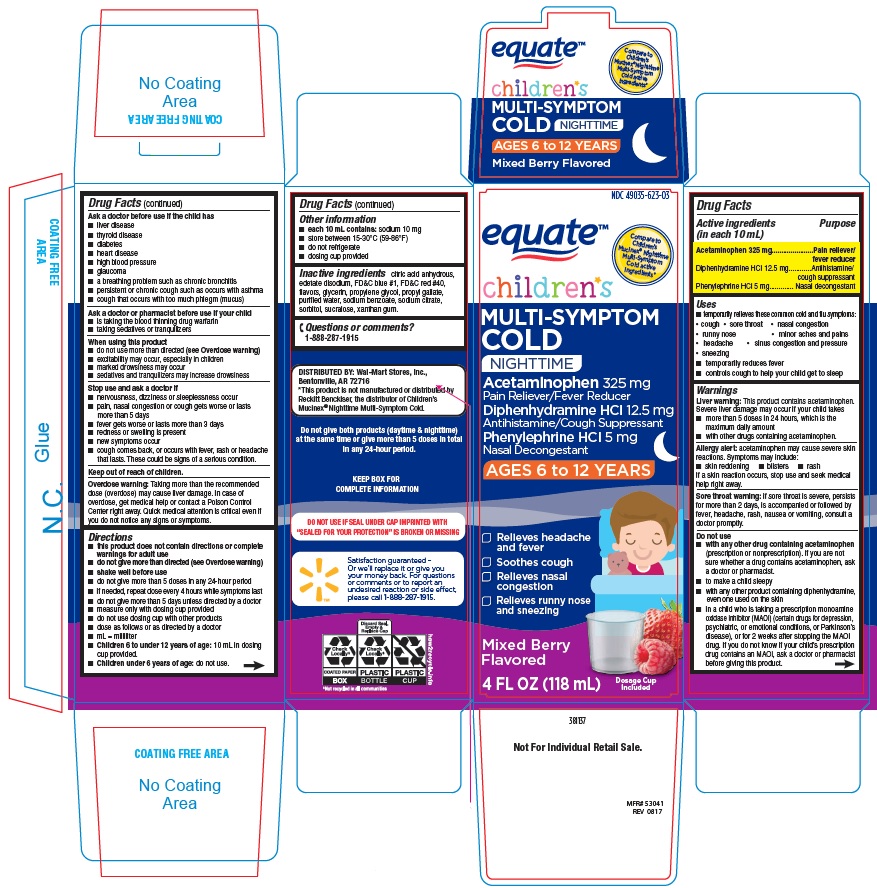 DRUG LABEL: Equate Childrens Multi symptom Cold Nighttime
NDC: 49035-623 | Form: LIQUID
Manufacturer: Wal-Mart Stores, Inc.
Category: otc | Type: Human OTC Drug Label
Date: 20241220

ACTIVE INGREDIENTS: ACETAMINOPHEN 325 mg/10 mL; DIPHENHYDRAMINE HYDROCHLORIDE 12.5 mg/10 mL; PHENYLEPHRINE HYDROCHLORIDE 5 mg/10 mL
INACTIVE INGREDIENTS: ANHYDROUS CITRIC ACID; EDETATE DISODIUM; FD&C BLUE NO. 1; FD&C RED NO. 40; GLYCERIN; PROPYLENE GLYCOL; PROPYL GALLATE; WATER; SODIUM BENZOATE; SODIUM CITRATE; SORBITOL; SUCRALOSE; XANTHAN GUM

Equate Children's Multi-Symptom Cold Nighttime

ACTIVE INGREDIENTS (in each 10 mL)

Acetaminophen 325 mg

Diphenhydramine HCl 12.5 mg

Phenyephrine HCl 5 mg

PURPOSE

Pain reliever / fever reducer

Antihistamine/Cough Suppressant

Nasal decongestant

USE(S)

temporarily relieves these common cold and flu symptoms:

- cough
- sore throat
- nasal congestion
- runny nose
- minor aches and pains
- headache
- sinus congestion and pressure
- sneezing
- temporarily reduces fever
- controls cough to help your child get to sleep

WARNINGS

Liver warning: This product contains acetaminophen. Severe liver damage may occur if your child takes

- more than 5 doses in 24 hous, which is the maximum daily amount
- with other drugs containing acetaminophen.

Allergy alert: acetaminophen may cause severe skin reactions. Symptoms may include:

- skin reddening
- blisters
- rash

If a skin reaction occurs, stop use and seek medical help right away
Sore throat warning: if sore throat is severe, persists for more than 2 days, is accompanied or followed by fever, headache, rash, nausea or vomiting, consult a doctor promptly.

DO NOT USE

- with any other drug containing acetaminophen (prescription or nonprescription). If you are not sure whether a drug contains acetaminophen, ask a doctor or pharmacist.
- to make a child sleepy
- with any other product containing diphenhydramine, even one used on the skin.
- in a child who is taking a prescription monoamine oxidase inhibitor (MAOI) (certain drugs for depression, psychiatric, or emotional conditions, or Parkinson's disease), or for 2 weeks after stopping the MAOI drug. If you do not know if your child's prescription drug contains an MAOI, ask a doctor or pharmacist before giving this product.

ASK A DOCTOR BEFORE USE IF THE CHILD HAS

- liver disease
- thyroid disease
- diabetes
- heart disease
- high blood pressure
- glaucoma
- a breathing problem such as chronic bronchitis
- persistent or chronic cough such as occurs with asthma
- cough that occurs with too much phlegm (mucus)

ASK A DOCTOR OR PHARMACIST BEFORE USE IF YOUR CHILD

- is taking the blood thinning drug warfarin
- taking sedatives or tranquilizers

WHEN USING THIS PRODUCT

- do not use more than directed (see Overdose warning)
- excitability may occur, especially in children
- marked drowsiness may occur
- sedatives and tranquilizers may increase dowsiness

STOP USE AND ASK DOCTOR IF

- nervousness, dizziness or sleeplessness occur
- pain, nasal congestion or cough gets worse or lasts more than 5 days
- fever gets worse or lasts more than 3 days
- redness or swelling is present
- new symptoms occur
- cough comes back, or occurs with rash or headache that lasts. These could be signs of a serious condition.

KEEP OUT OF REACH OF CHILDREN

Overdose warning: Taking more than the recommended dose (overdose) may cause liver damage. In case of overdose, get medical help or contact a Poison Control Center right away. Quick medical attention is critical even if you do not notice any signs or symptoms.

DIRECTIONS

- this product does not contain directions or complete warnings for adult use
- do not give more than directed (see Overdose warning)
- shake well before use
- do not give more than 5 doses in any 24-hour period
- if needed, repeat dose every 4 hours while symptoms last
- do not give more than 5 days unless directed by a doctor
- measure only with dosing cup provided
- do not use dosing cup with other products
- dose as follows or as directed by a doctor
- mL = milliliter
- Children 6 to under 12 years of age: 10 mL in dosing cup provided.
- Children under 6 years of age: do not use.

OTHER INFORMATION

- each 10 mL contains: sodium 10 mg
- store between 15-30°C (59-86°F)
- do not refrigerate
- dosing cup provided

INACTIVE INGREDIENTS

citric acid anhydrous, edetate disodium, FD&C blue #1, FD&C red #40, flavors, glycerin, propylene glycol, propyl gallate, purified water, sodium benzoate, sodium citrate, sorbitol, sucralose, xanthan gum.

QUESTIONS OR COMMENTS

1-888-287-1915

PRINCIPAL DISPLAY PANEL

NDC 49035-623-03

equate

Compare to Children's Mucinex® Nighttime Multi-Symptom Cold active ingredients*

Children's

MULTI-SYMPTOMS COLD
NIGHTTIME

Acetaminophen 325 mg
Pain reliever/Fever Reducer

Diphenhydramine HCl 12.5 mg

Antihistamine/Cough Suppressant

Phenylephrine HCl 5 mg

Nasal Decongestant
AGES 6 to 12 YEARS

- Relieves headache and fever
- Soothes cough
- Relieves nasal congestion
- Relieves runny nose and sneezing

Mixed Berry Flavored

4 FL OZ (118 mL)